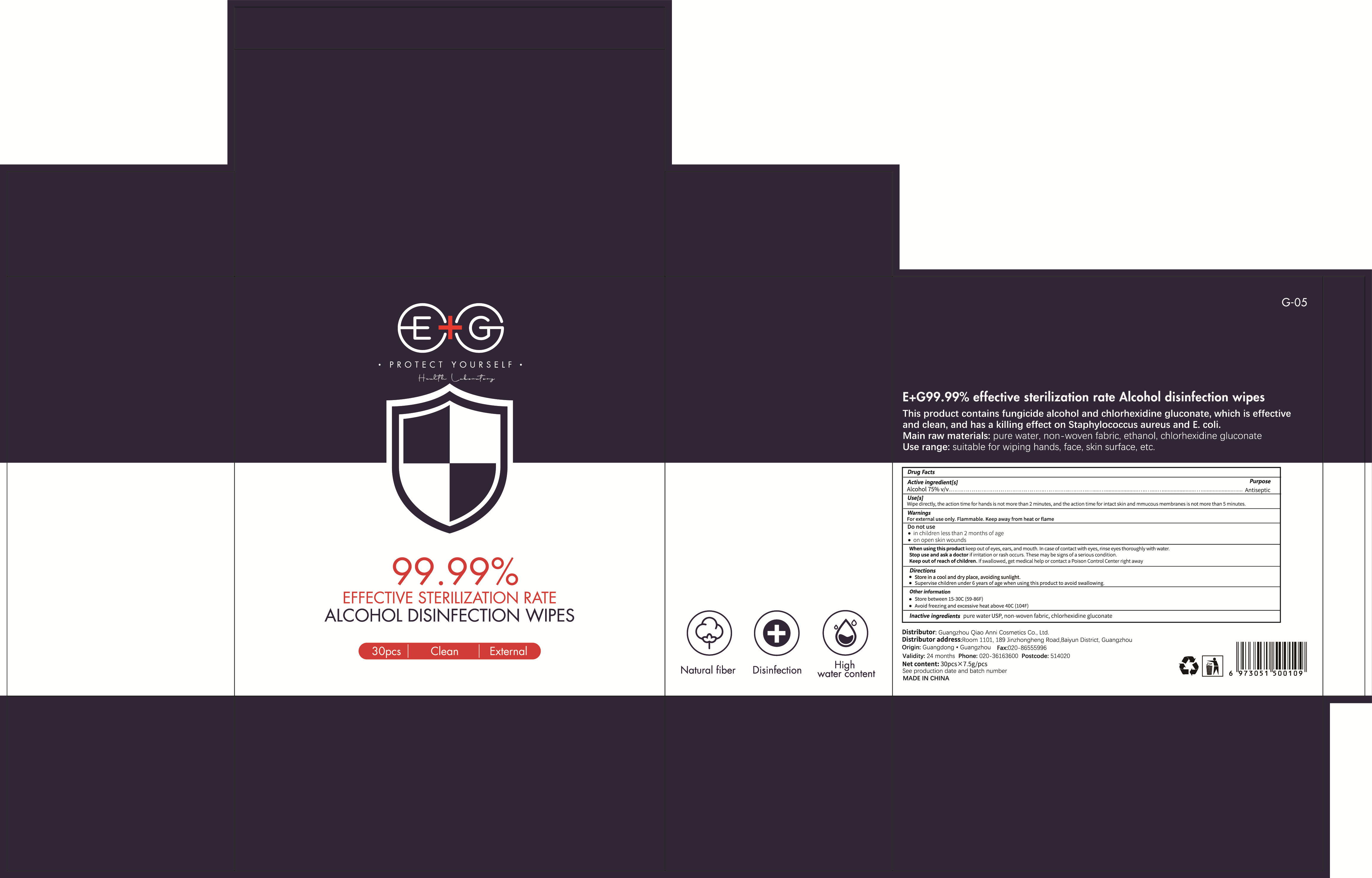 DRUG LABEL: E G99.99% effective sterilization rate Alcohol disinfection wipes
NDC: 68923-006 | Form: CLOTH
Manufacturer: Guangzhou Qiao Anni Cosmetics Co., Ltd.
Category: otc | Type: HUMAN OTC DRUG LABEL
Date: 20200608

ACTIVE INGREDIENTS: ALCOHOL 168.75 g/30 1
INACTIVE INGREDIENTS: WATER; CHLORHEXIDINE GLUCONATE

DOSAGE AND ADMINISTRATION

Store between 15 -30°C (59-86°F)

INACTIVE INGREDIENT

pure water USP, non-woven fabric,chlorhexidine gluconate

INDICATIONS AND USAGE

Wipe directly, the action time for hands is not more than 2 minutes, and the action time for intact skin and mmucous membranes is not more than 5 minutes

ACTIVE INGREDIENT

Alcohol

keep out of reach of children

PURPOSE

Disinfection
Sterilization
No Rinseing

WARNINGS

For external use only. Flammable. Keep away from heat or flame